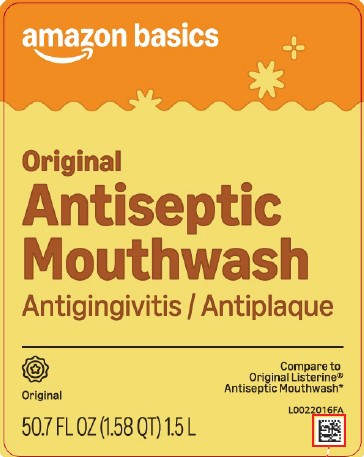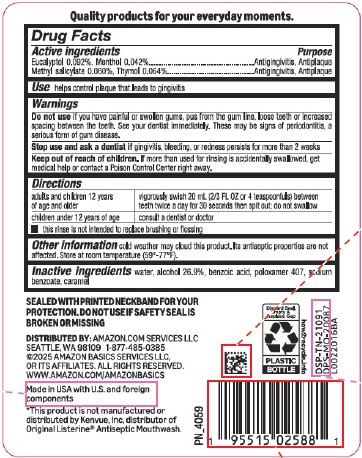 DRUG LABEL: Original Antiseptic
NDC: 72288-318 | Form: MOUTHWASH
Manufacturer: Amazon.Com Services LLC
Category: otc | Type: HUMAN OTC DRUG LABEL
Date: 20250915

ACTIVE INGREDIENTS: EUCALYPTOL 0.92 mg/1 mL; MENTHOL 0.42 mg/1 mL; METHYL SALICYLATE 0.6 mg/1 mL; THYMOL 0.64 mg/1 mL
INACTIVE INGREDIENTS: WATER; ALCOHOL; BENZOIC ACID; POLOXAMER 407; SODIUM BENZOATE; CARAMEL

Basics 318.003/318AH-AI
Antiseptic Mouthrinse

Claim

Quality products for your everyday moments.

Active Ingredients

Eucalyptol 0.092%

Menthol 0.042%

Methyl salicylate 0.060%

Thymol 0.064%

Purpose

Antigingivitis, Antiplaque

Use

helps control plaque that leads to gingivitis

Warnings

for this product

Do Not Use

if you have painful or swollen gums, pus from the gum line, loose teeth or increased spacing between the teeth. See your dentist immediately. These may be signs of periodontitis, a serious form of gum disease.

Stop use and ask a dentist if

gingivitis, bleeding, or redness persists for more than 2 weeks

Keep out of reach of children.

If more than used for rinsing is accidentally swallowed, get medical help or contact a Poison Control Center right away.

Directions

adults and children 12 years of age and older - vigorously swish 20 mL (2/3 FL OZ or 4 teaspoonfuls) between teeth twice a day for 30 seconds then spit out; do not swallow

children under 12 years of age - consult a dentist or doctor

- this rinse is not intended to replace brushing or flossing

Other information

cold weather may cloud this product. Its antiseptic properties are not affected. Store at room temperature (59°-77°F).

Inactive ingredients

water, alcohol 26.9%, benzoic acid, poloxamer 407, sodium benzoate, caramel

Tamper Evident Statement

SEALED WITH PRINTED NECKBAND FOR YOUR PROTECTION. DO NOT USE IF SAFETY SEAL IS BROKEN OR MISSING.

Disclaimer

*This product is not manufactured or distributed by Kenvue, Inc., distributor of Original ListerineAntiseptic Mouthwash.

ADVERSE REACTION

DISTRIBUTED BY: Amazon.com, Services, LLC

Seattle, WA 98109 1-877-485-0385

©2025 Amazon Basics Services LLC, or its affiliates.

All rights reserved.

www.amazon.com/amazonbasics

Made in USA with U.S. and foreign components.

DSP-TN-21091

DSP-MO-20087

Discard Seal, Empty & Replace Cap

PLASTIC BOTTLE

how2recycle.info

Principal display panel

amazon basics

Original

Antiseptic

Mouthwash

Antigingivitis / Antiplaque

Original

Compare to Original Listerine® Antiseptic Mouthwash*

50.7 FL OZ (1.58 QT) 1.5 L